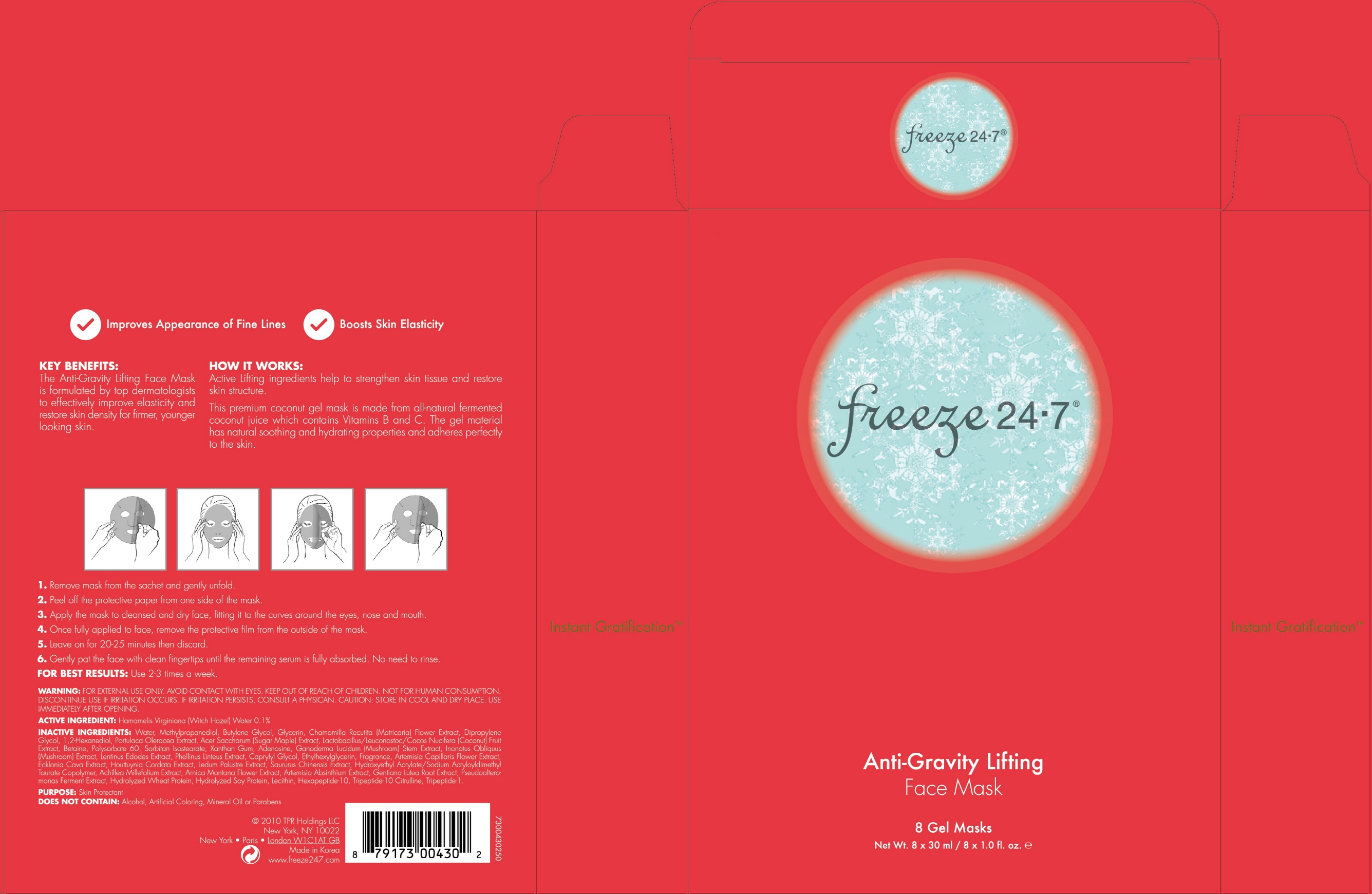 DRUG LABEL: Freeze 24 7 Anti Gravity Lifting Face Mask
NDC: 70592-030 | Form: PATCH
Manufacturer: Summit C&T LLC
Category: otc | Type: HUMAN OTC DRUG LABEL
Date: 20160407

ACTIVE INGREDIENTS: Witch Hazel 0.03 g/30 mL
INACTIVE INGREDIENTS: Water; Methylpropanediol

ACTIVE INGREDIENT

Active Ingredient: Hamamelis Virginiana (Witch Hazel) Water 0.1%

INACTIVE INGREDIENT

Inactive Ingredients: Water, Methylpropanediol, Butylene Glycol, Glycerin, Chamomilla Recutita (Matricaria) Flower Extract, Dipropylene Glycol, 1,2-Hexanediol, Portulaca Oleracea Extract, Acer Saccharum (Sugar Maple) Extract, Lactobacillus/Leuconostoc/Cocos Nucifera (Coconut) Fruit Extract, Betaine, Polysorbate 60, Sorbitan Isostearate, Xanthan Gum, Adenosine, Ganoderma Lucidum (Mushroom) Stem Extract, Inonotus Obliquus (Mushroom) Extract, Lentinus Edodes Extract, Phellinus Linteus Extract, Caprylyl Glycol, Ethylhexylglycerin, Fragrance, Artemisia Capillaris Flower Extract, Ecklonia Cava Extract, Houttuynia Cordata Extract, Ledum Palustre Extract, Saururus Chinensis Extract, Hydroxyethyl Acrylate/Sodium Acryloyldimethyl Taurate Copolymer, Achillea Millefolium Extract, Arnica Montana Flower Extract, Artemisia Absinthium Extract, Gentiana Lutea Root Extract, Pseudoalteromonas Ferment Extract, Hydrolyzed Wheat Protein, Hydrolyzed Soy Protein, Lecithin, Hexapeptide-10, Tripeptide-10 Citrulline, Tripeptide-1

PURPOSE

Purpose: Skin protectant

WARNINGS

Warnings: For external use only. Avoid contact with eyes. Not for human consumption. Discontinue use if irritation occurs. If irritation persists, consult a physician. Use immediately after opening. Caution: Store in cool and dry place. Use Immediately after opening.

KEEP OUT OF REACH OF CHILDREN

INDICATIONS & USAGE

How to use: 1. Remove mask from the sachet and gently unfold. 2. Peel off the protective paper from one side of the mask. 3. Apply the mask to cleansed and dry face, fitting it to the curves around the eyes, nose and mouth. 4. Once fully applied to face, remove the protective film from the outside of the mask. 5. Leave on for 20-25 minutes then discard. 6. Gently pat the face with clean fingertips until the remaining serum is fully absorbed. No need to rinse.

DOSAGE & ADMINISTRATION

For Best Results: Use 2-3 times a week.